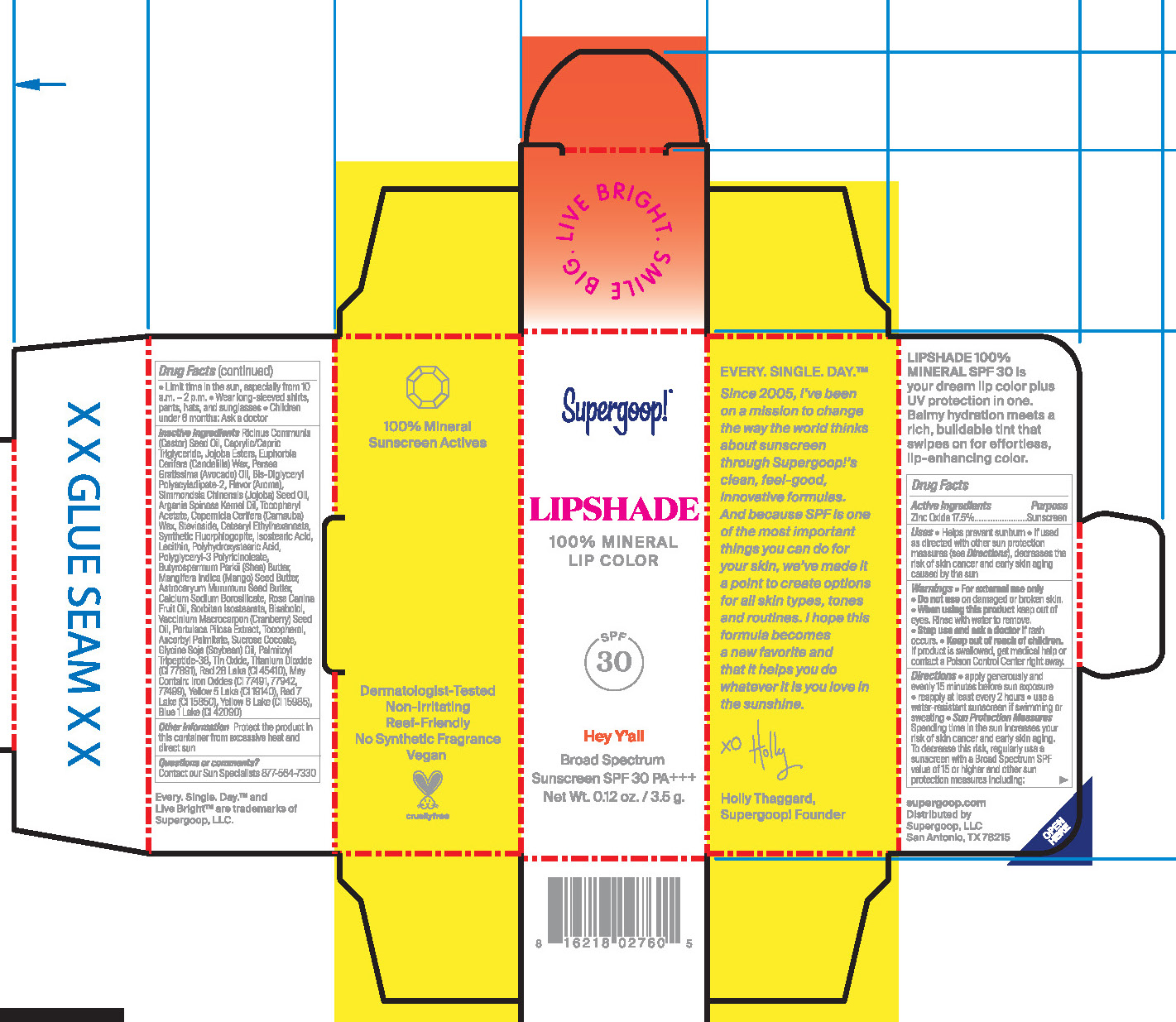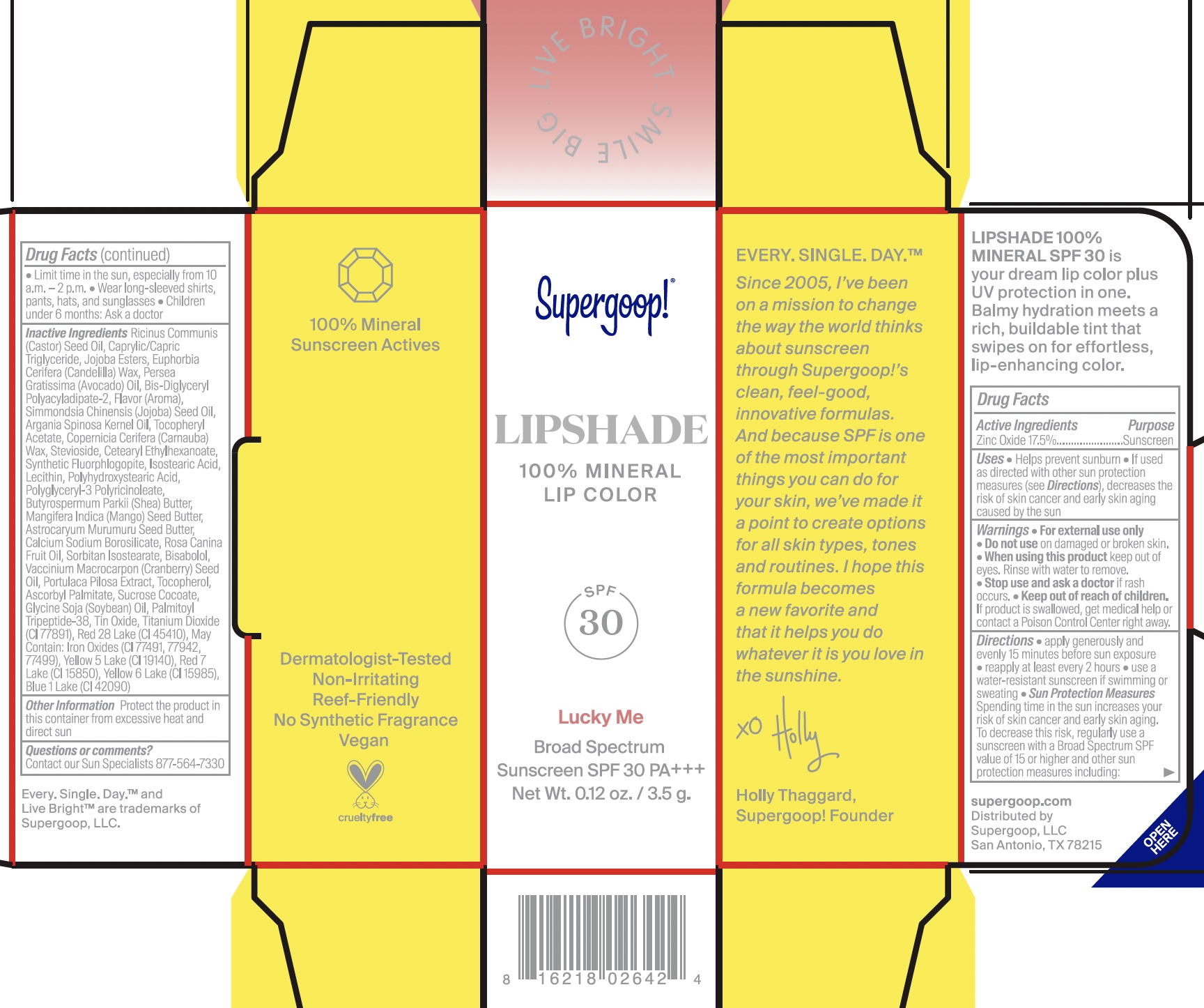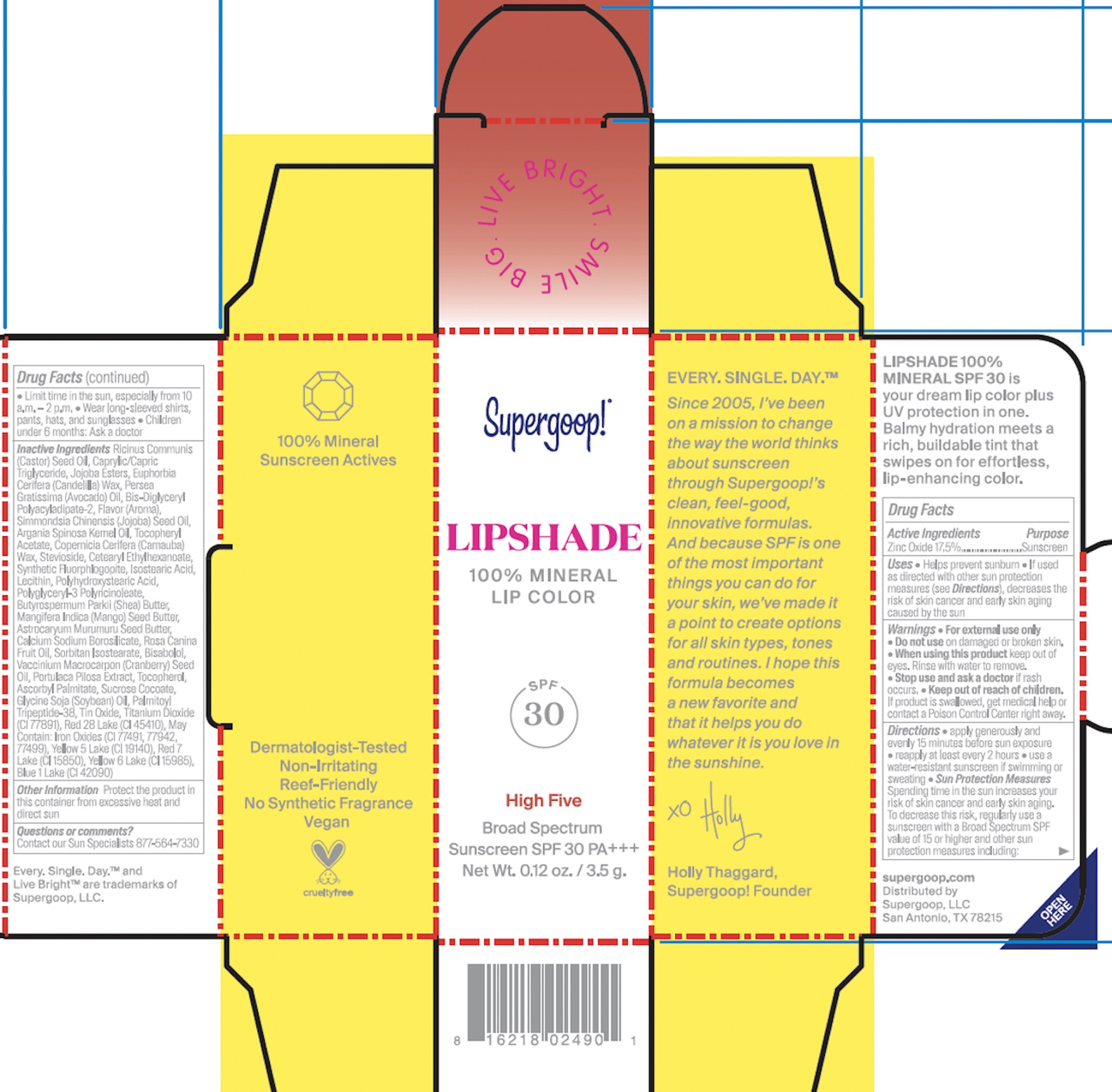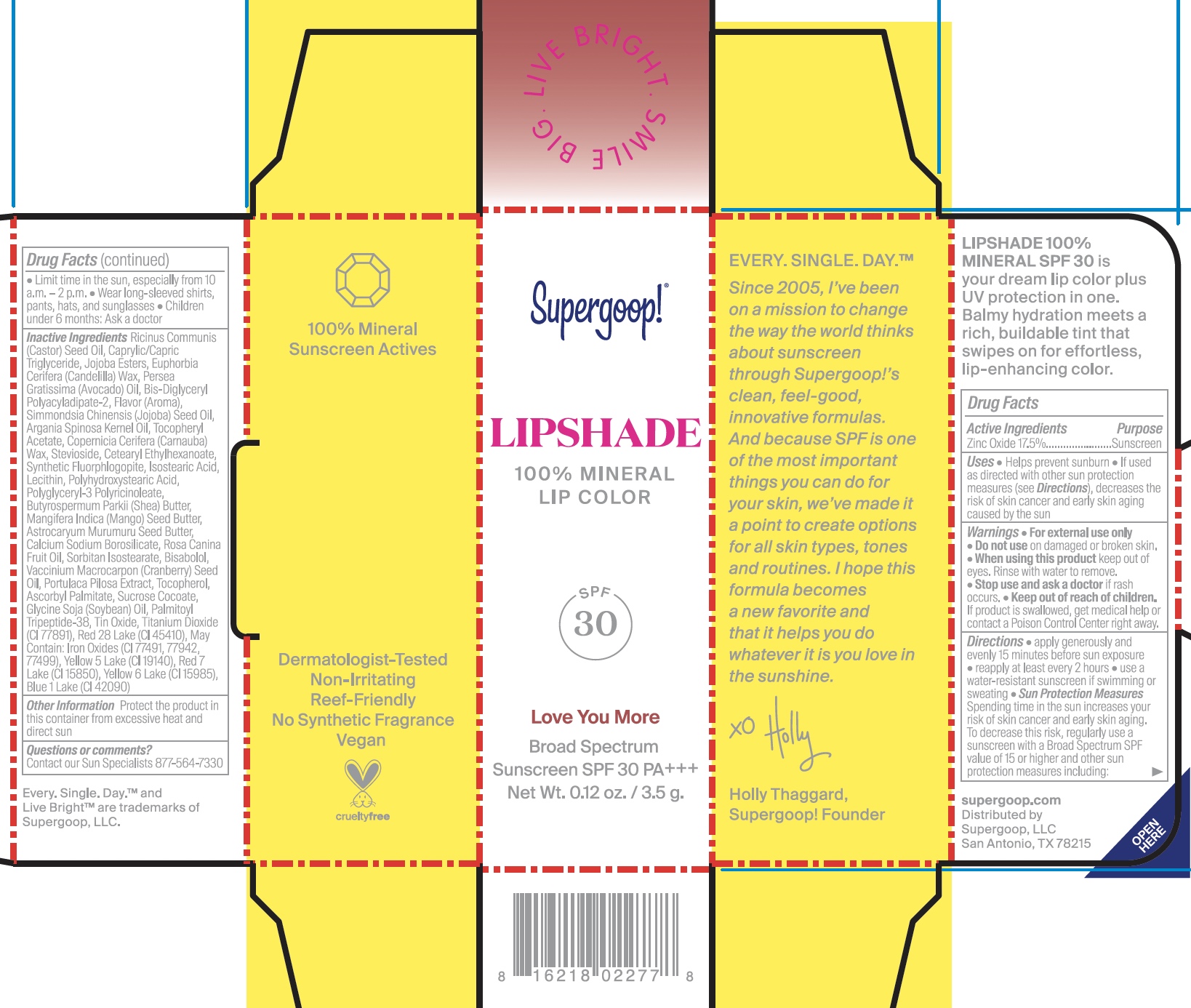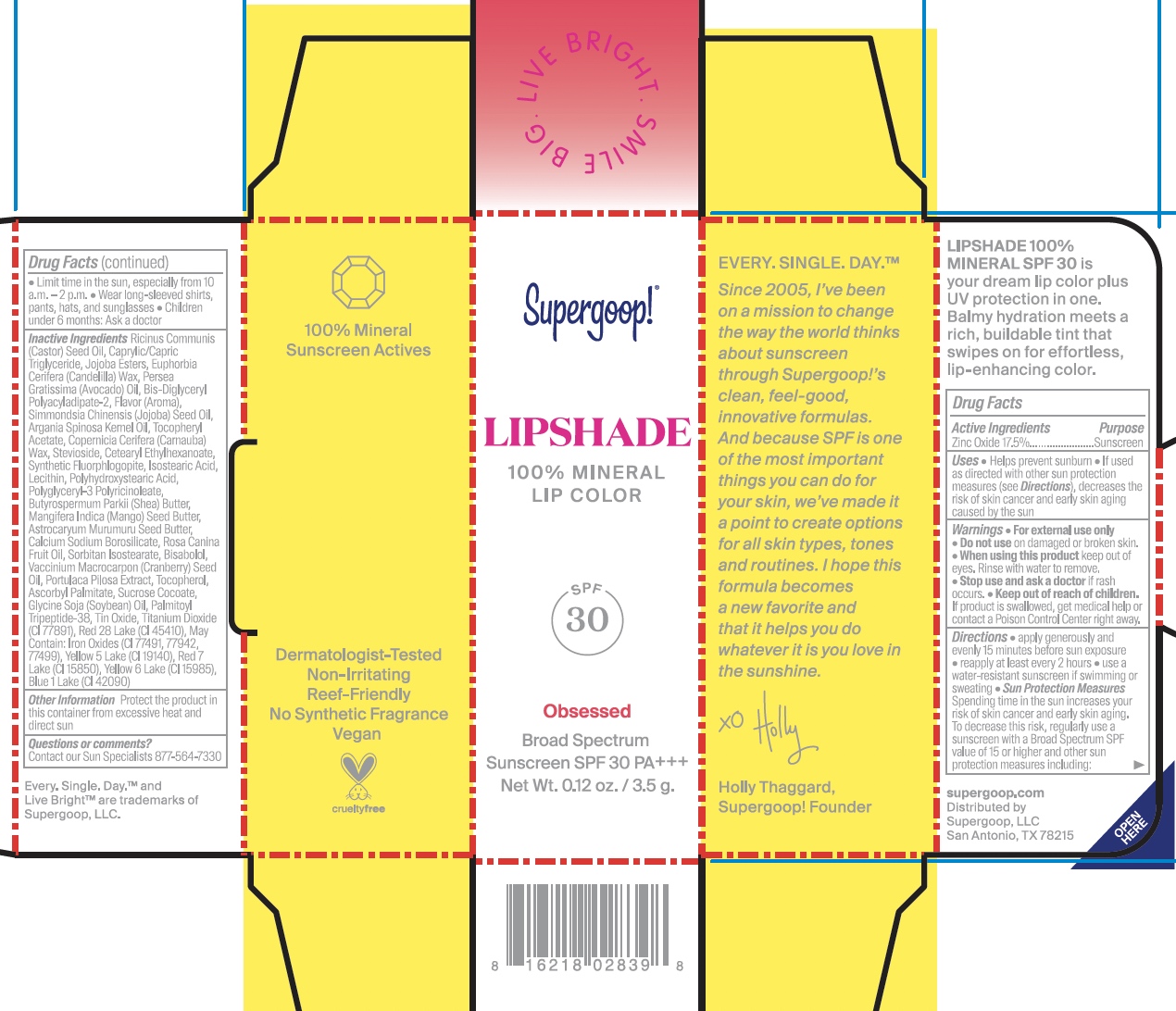 DRUG LABEL: Lipshade SPF 30 High Five
NDC: 75936-616 | Form: LIPSTICK
Manufacturer: Supergoop, LLC
Category: otc | Type: HUMAN OTC DRUG LABEL
Date: 20241205

ACTIVE INGREDIENTS: ZINC OXIDE 17.5 g/100 g
INACTIVE INGREDIENTS: FERRIC OXIDE RED; MANGIFERA INDICA SEED BUTTER; SORBITAN ISOSTEARATE; TOCOPHEROL; ASCORBYL PALMITATE; MAGNESIUM POTASSIUM ALUMINOSILICATE FLUORIDE; ISOSTEARIC ACID; LECITHIN, SOYBEAN; POLYGLYCERYL-3 PENTARICINOLEATE; PEPPERMINT; STEVIOSIDE; CETEARYL ETHYLHEXANOATE; PALMITOYL LYSYLDIOXYMETHIONYLLYSINE; STANNIC OXIDE; TITANIUM DIOXIDE; ROSA CANINA FRUIT OIL; MEDIUM-CHAIN TRIGLYCERIDES; JOJOBA OIL, RANDOMIZED; CRANBERRY SEED OIL; PORTULACA PILOSA WHOLE; AVOCADO OIL; SUCROSE COCOATE; SOYBEAN OIL; D&C RED NO. 28; RICINUS COMMUNIS SEED; ARGAN OIL; POLYHYDROXYSTEARIC ACID (2300 MW); BUTYROSPERMUM PARKII (SHEA) BUTTER UNSAPONIFIABLES; .ALPHA.-TOCOPHEROL ACETATE; ASTROCARYUM MURUMURU SEED BUTTER; LEVOMENOL; CALCIUM ALUMINUM BOROSILICATE; CANDELILLA WAX; BIS-DIGLYCERYL POLYACYLADIPATE-2; CARNAUBA WAX; FD&C YELLOW NO. 6; FD&C YELLOW NO. 5; FD&C BLUE NO. 1; FERROSOFERRIC OXIDE; D&C RED NO. 6; FERRIC OXIDE YELLOW

Lipshade SPF 30

Active Ingredients: Zinc Oxide 17.5%

PURPOSE

Helps prevent sunburn

If used as directed with other sun protection measures (see Directions), decreases the risk of skin cancer and early skin aging caused by the sun

Keep out of reach of children. If product is swallowed, get medical help, or contact a poison control center right away.

WARNINGS

For External use only

Do not use on damaged or broken skin

When using this product, keep out of eyes. Rinse with water to remove

Stop use and ask a doctor if rash occurs

Directions

Apply generously and evenly 15 minutes before sun exposure

Reapply (will vary depending on WR)

after XX minutes of swimming or sweating

Immediately after towel drying

at least every 2 hours

Sun Protection Measures: Spending time in the sun increases your risk of skin cancer and early skin aging. To decrease this risk, regularly use a sunscreen with a Broad Spectrum SPF value of 15 or higher and other sun protection measures including:

Limit time in the sun, especially from 10 a.m.- 2 p.m.

Wear long-sleeved shirts, pants, hats, and sunglasses

Children under 6 months: Ask a doctor

INACTIVE INGREDIENT

Argania Spinosa Kernel Oil, Ascorbyl Palmitate, Astrocaryum Murumuru Seed Butter, Bis-Diglyceryl Polyacyladipate-2, Bisabolol, Butyrospermum Parkii (Shea) Butter, Calcium Sodium Borosilicate, Caprylic/Capric Triglyceride, Cetearyl Ethylhexanoate, CI 42090, CI 77491, CI 77492, CI 77499, CI 77891, Copernicia Cerifera (Carnauba) Wax, D-Alpha Tocopherol, D&C Red No. 28, D&C Red No. 7, Dl-Alpha-Tocopherol, Euphorbia Cerifera (Candelilla) Wax, Farnesol, Flavor (Aroma), Glycine Soja (Soybean) Oil, Isostearic Acid, Jojoba Esters, Lecithin, Limonene, Mangifera Indica (Mango) Seed Butter, Palmitoyl Tripeptide-38, Persea Gratissima (Avocado) Oil, Polyglyceryl-3 Polyricinoleate, Polyhydroxystearic Acid, Portulaca Pilosa Extract, Ricinus Communis (Castor) Seed Oil, Rosa Canina Fruit Oil, Simmondsia Chinensis (Jojoba) Seed Oil, Sorbitan Isostearate, Stevioside, Sucrose Cocoate, Synthetic Fluorphlogopite, Tin Dioxide, Tocopherols Concentrate - Mixed (High Alpha Type), Vaccinium Macrocarpon (Cranberry) Seed Oil, Yellow 5 Lake, Yellow 6 Lake.

Hey Yall

LIPSHADE

100% Mineral

Lip Color

SPF 30

Hey Y'all

High Five

LIPSHADE

100% Mineral

Lip Color

SPF30

High Five

Love You More

LIPSHADE

100%

Lip Color

SPF 30

Love you more

Lucky Me

LIPSHADE

100% Mineral

Lip Color

SPF 30

Lucky Me

Obsessed

LIPSHADE

100% Mineral

Lip Color

SPF 30

Obsessed